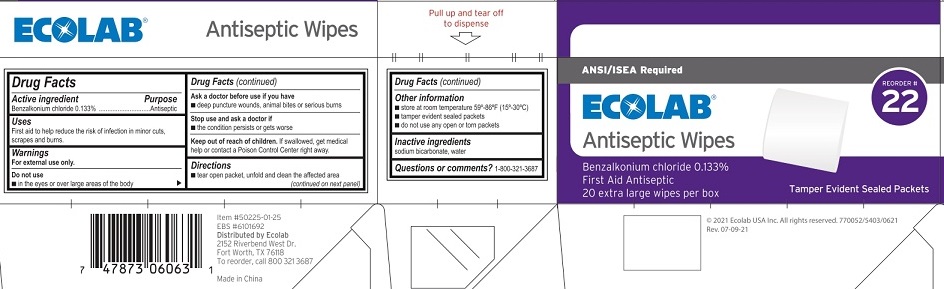 DRUG LABEL: ECOLAB Antiseptic
NDC: 71338-225 | Form: LIQUID
Manufacturer: Ecolab Food Safety Specialties, Inc.
Category: otc | Type: HUMAN OTC DRUG LABEL
Date: 20250909

ACTIVE INGREDIENTS: BENZALKONIUM CHLORIDE 1.33 mg/1 mL
INACTIVE INGREDIENTS: WATER; SODIUM BICARBONATE

Ecolab Antiseptic Wipes

Drug Facts

Active ingredient

Benzalkonium Chloride, 0.133%

Purpose

Antiseptic

Uses

First aid to help reduce the risk of infection in minor cuts, scrapes and burns.

Warnings

For external use only.

Do not use

- in the eyes or over large areas of the body

Ask a doctor before use if you have

- deep punture wounds, animal bites or serious burns

Stop use and ask a doctor if

- if the condition persists or gets worse

Keep out of reach of children. If swallowed, get medical help or contact a Poison Control Center right away.

Directions

- tear open packet, unfold and clean the affected area

Other information

- store at room temperature 59°-86°F (15°-30°C)
- tamper evident sealed packets
- do not use any open or torn packets

Inactive ingredients

sodium bicarbonate, water

Questions or comments?

1-800-321-3687

PACKAGE LABEL

ANSI/ISEA Required

Ecolab® Antiseptic Wipes

Reorder # 22

Benzalonium chloride 0.133%

First Aid Antiseptic

20 extra large wipes per box

Tamper Evident Sealed Packets